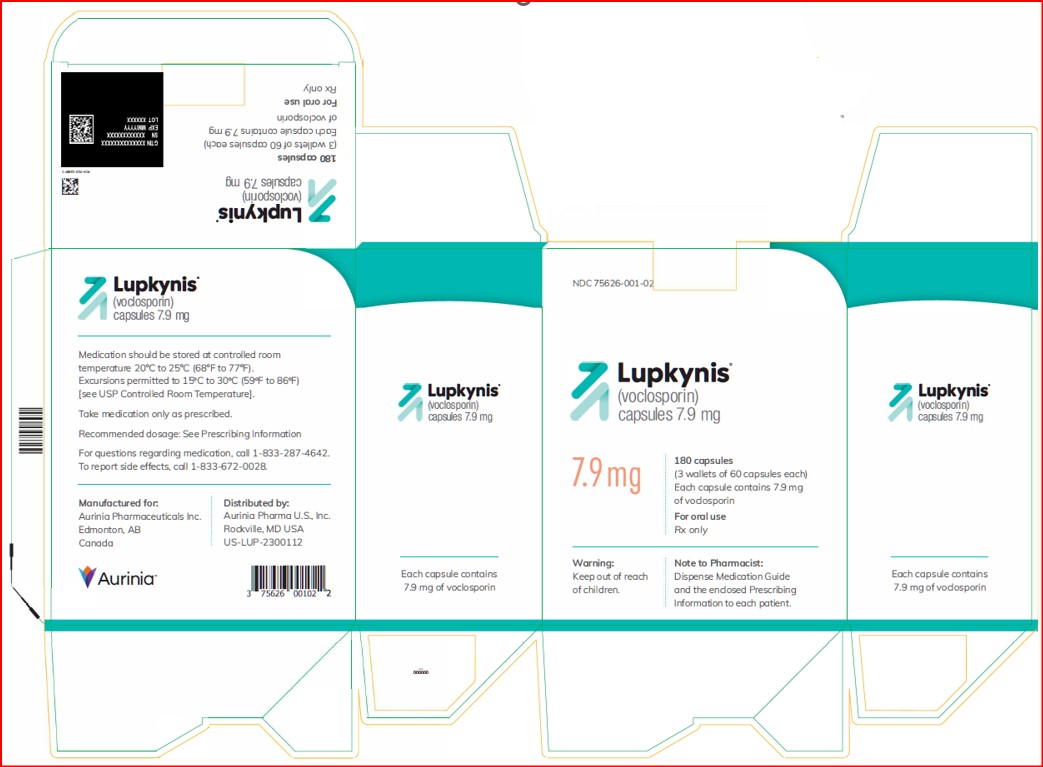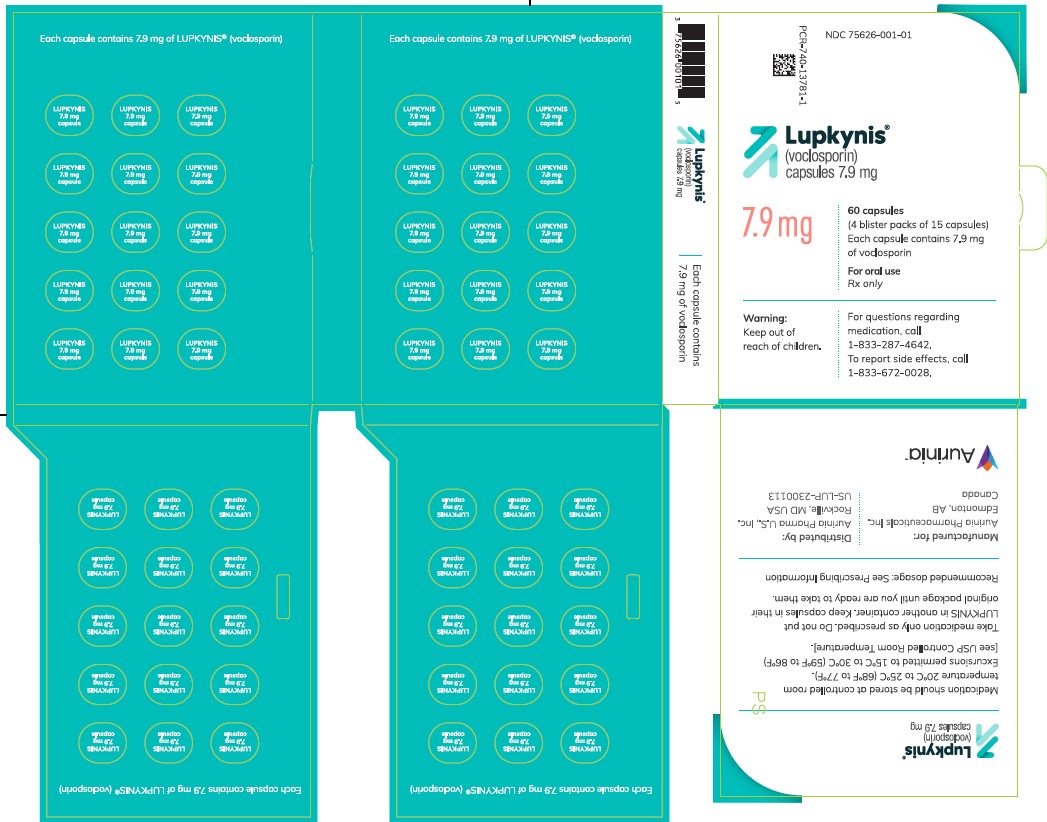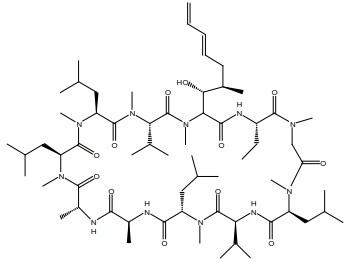 DRUG LABEL: LUPKYNIS
NDC: 75626-001 | Form: CAPSULE
Manufacturer: Aurinia Pharma U.S., Inc.
Category: prescription | Type: HUMAN PRESCRIPTION DRUG LABEL
Date: 20251008

ACTIVE INGREDIENTS: VOCLOSPORIN 7.9 mg/1 1
INACTIVE INGREDIENTS: ALCOHOL; POLYSORBATE 40; MEDIUM-CHAIN TRIGLYCERIDES; TOCOPHERSOLAN

HIGHLIGHTS OF PRESCRIBING INFORMATION

These highlights do not include all the information needed to use LUPKYNIS® safely and effectively. See full prescribing information for LUPKYNIS.
LUPKYNIS (voclosporin) capsules, for oral use
Initial U.S. Approval: 2021

WARNING: MALIGNANCIES AND SERIOUS INFECTIONS

See full prescribing information for complete boxed warning.
Increased risk for developing serious infections and malignancies with LUPKYNIS or other immunosuppressants that may lead to hospitalization or death. (5.1, 5.2)

RECENT MAJOR CHANGES

Warnings and Precautions, Hypersensitivity Reactions (5.8) 10/2025

1 INDICATIONS AND USAGE

LUPKYNIS is a calcineurin-inhibitor immunosuppressant indicated in combination with a background immunosuppressive therapy regimen for the treatment of adult patients with active lupus nephritis (LN). (1, 14)

Limitations of Use: Safety and efficacy of LUPKYNIS have not been established in combination with cyclophosphamide. Use of LUPKYNIS is not recommended in this situation.

2 DOSAGE AND ADMINISTRATION

Administration:

- LUPKYNIS must be swallowed whole on an empty stomach. (2.1)
- Administer consistently as close to a 12-hour schedule as possible, and with at least 8 hours between doses. (2.1)
- If a dose is missed, instruct the patient to take it as soon as possible within 4 hours after missing the dose. Beyond the 4-hour time frame, instruct the patient to wait until the usual scheduled time to take the next regular dose. Instruct the patient not to double the next dose. (2.1)
- Instruct patients to avoid eating grapefruit or drinking grapefruit juice while taking LUPKYNIS. (2.1, 7.1)

Dosage Recommendations:

- Before initiating LUPKYNIS, establish an accurate baseline estimated glomerular filtration rate (eGFR) and check blood pressure (BP).
  - Use of LUPKYNIS is not recommended in patients with a baseline eGFR ≤45 mL/min/1.73 m^2 unless the benefit exceeds the risk; these patients may be at increased risk for acute and/or chronic nephrotoxicity. (2.2, 5.3)
  - Do not initiate LUPKYNIS in patients with baseline BP >165/105 mmHg or with hypertensive emergency. (2.2, 5.4)
- Recommended starting dose: 23.7 mg orally, twice a day. (2.3)
- Use LUPKYNIS in combination with mycophenolate mofetil (MMF) and corticosteroids. (2.3)
- Modify the LUPKYNIS dose based on eGFR (2.3, 5.3):
  - Assess eGFR every two weeks for the first month, every four weeks through the first year, and quarterly thereafter.
  - If eGFR <60 mL/min/1.73 m^2 and reduced from baseline by >20% and <30%, reduce the dose by 7.9 mg twice a day. Re-assess eGFR within two weeks; if eGFR is still reduced from baseline by >20%, reduce the dose again by 7.9 mg twice a day.
  - If eGFR <60 mL/min/1.73 m^2 and reduced from baseline by ≥30%, discontinue LUPKYNIS. Re-assess eGFR within two weeks; consider re-initiating LUPKYNIS at a lower dose (7.9 mg twice a day) only if eGFR has returned to ≥80% of baseline.
  - For patients that had a decrease in dose due to eGFR, consider increasing the dose by 7.9 mg twice a day for each eGFR measurement that is ≥80% of baseline; do not exceed the starting dose.
- Monitor blood pressure every two weeks for the first month after initiating LUPKYNIS, and as clinically indicated thereafter. For patients with BP >165/105 mmHg or with hypertensive emergency, discontinue LUPKYNIS and initiate antihypertensive therapy. (2.3, 5.4)
- If the patient has not experienced therapeutic benefit by 24 weeks, consider discontinuation of LUPKYNIS. (2.3)

Dosage Adjustments:

- Patients with severe renal impairment: the recommended dose is 15.8 mg twice daily. (2.4, 8.6)
- Patients with mild and moderate hepatic impairment: the recommended dose is 15.8 mg twice daily. (2.4, 8.7)

3 DOSAGE FORMS AND STRENGTHS

Capsules: 7.9 mg (3)

4 CONTRAINDICATIONS

- Patients concomitantly using strong CYP3A4 inhibitors (e.g., ketoconazole, itraconazole, clarithromycin). (4)
- History of serious or severe hypersensitivity reaction, including anaphylaxis, to LUPKYNIS or any of its excipients. (4)

5 WARNINGS AND PRECAUTIONS

- Nephrotoxicity (acute and/or chronic): May occur due to LUPKYNIS or concomitant nephrotoxic drugs. Monitor renal function; consider dosage reduction. (5.3)
- Hypertension: May require antihypertensive therapy; monitor relevant drug interactions. (5.4)
- Neurotoxicity: Including risk of posterior reversible encephalopathy syndrome (PRES); monitor for neurologic abnormalities; reduce dosage or discontinue LUPKYNIS. (5.5)
- Hyperkalemia: Risk may be increased with other agents associated with hyperkalemia; monitor serum potassium levels. (5.6)
- QT Prolongation: Consider obtaining electrocardiograms and monitoring electrolytes in patients at high risk. (5.7)
- Hypersensitivity Reactions: Discontinue LUPKYNIS; treat and monitor until signs and symptoms resolve. (5.8)
- Immunizations: Avoid live vaccines. (5.9)
- Pure Red Cell Aplasia: Consider discontinuation. (5.10)

6 ADVERSE REACTIONS

The most commonly reported adverse reactions (≥3%) were: glomerular filtration rate decreased, hypertension, diarrhea, headache, anemia, cough, urinary tract infection, abdominal pain upper, dyspepsia, alopecia, renal impairment, abdominal pain, mouth ulceration, fatigue, tremor, acute kidney injury, and decreased appetite. (6.1)

To report SUSPECTED ADVERSE REACTIONS, contact Aurinia Pharmaceuticals at 1-833-672-0028 or FDA at 1-800-FDA-1088 or www.fda.gov/medwatch.

7 DRUG INTERACTIONS

- Moderate CYP3A4 inhibitors: Reduce LUPKYNIS daily dosage to 15.8 mg in the morning and 7.9 mg in the evening. (2.5, 7.1, 12.3)
- Strong and moderate CYP3A4 inducers: Avoid co-administration. (7.1, 12.3)
- Certain P-gp substrates: Reduce dosage of certain P-gp substrates with a narrow therapeutic window when co-administered with LUPKYNIS. (7.2, 12.3)

8 USE IN SPECIFIC POPULATIONS

- Pregnancy: May cause fetal harm. (8.1)
- Renal Impairment: Use of LUPKYNIS is not recommended in patients with a baseline eGFR ≤45 mL/min/1.73 m^2 unless the benefit exceeds the risk. If used in patients with severe renal impairment at baseline, LUPKYNIS should be used at a reduced dose. (2.4, 8.6)
- Hepatic Impairment:
  - Mild and moderate hepatic impairment: Dose reduction is required.
  - Severe hepatic impairment: Avoid LUPKYNIS use. (2.4, 8.7)

FULL PRESCRIBING INFORMATION

WARNING: MALIGNANCIES AND SERIOUS INFECTIONS

Increased risk for developing malignancies and serious infections with LUPKYNIS or other immunosuppressants that may lead to hospitalization or death [see Warnings and Precautions (5.1, 5.2)].

1 INDICATIONS AND USAGE

LUPKYNIS is indicated in combination with a background immunosuppressive therapy regimen [see Clinical Studies (14)] for the treatment of adult patients with active lupus nephritis (LN).

Limitations of Use: Safety and efficacy of LUPKYNIS have not been established in combination with cyclophosphamide. Use of LUPKYNIS is not recommended in this situation.

2 DOSAGE AND ADMINISTRATION

2.1 Important Administration Instructions

- LUPKYNIS capsules must be swallowed whole and must not be opened, crushed, or divided.
- LUPKYNIS should be taken on an empty stomach consistently as close to a 12-hour schedule as possible, and with a minimum of 8 hours between doses.
- If a dose is missed, instruct the patient to take it as soon as possible within 4 hours after missing the dose. Beyond the 4-hour time frame, instruct the patient to wait until the usual scheduled time to take the next regular dose. Instruct the patient not to double the next dose.
- Instruct patients to avoid eating grapefruit or drinking grapefruit juice while taking LUPKYNIS [see Drug Interactions (7.1)] .

2.2 Prior to Initiating LUPKYNIS Therapy

Establish an accurate baseline estimated glomerular filtration rate (eGFR). Use of LUPKYNIS is not recommended in patients with a baseline eGFR ≤45 mL/min/1.73 m^2 unless the benefit exceeds the risk; these patients may be at increased risk for acute and/or chronic nephrotoxicity [see Warnings and Precautions (5.3)] .

Check blood pressure (BP) at baseline. Do not initiate LUPKYNIS in patients with BP >165/105 mmHg or with hypertensive emergency [see Warnings and Precautions (5.4)] .

2.3 Dosage Recommendations

The recommended starting dose of LUPKYNIS is 23.7 mg twice a day.

Use LUPKYNIS in combination with mycophenolate mofetil (MMF) and corticosteroids [see Clinical Studies (14)] .

Safety and efficacy of LUPKYNIS have not been established in combination with cyclophosphamide. Use of LUPKYNIS is not recommended in this situation.

- Assess eGFR every two weeks for the first month, every four weeks through the first year and quarterly thereafter.

Dosage of LUPKYNIS is based on the patient’s eGFR. Modify LUPKYNIS dosage based on eGFR [see Warnings and Precautions (5.3)] :

- If eGFR <60 mL/min/1.73 m^2 and reduced from baseline by >20% and <30%, reduce the dose by 7.9 mg twice a day. Re-assess eGFR within two weeks; if eGFR is still reduced from baseline by >20%, reduce the dose again by 7.9 mg twice a day.
- If eGFR <60 mL/min/1.73 m^2 and reduced from baseline by ≥30%, discontinue LUPKYNIS. Re-assess eGFR within two weeks; consider re-initiating LUPKYNIS at a lower dose (7.9 mg twice a day) only if eGFR has returned to ≥80% of baseline.
- For patients that had a decrease in dose due to eGFR, consider increasing the dose by 7.9 mg twice a day for each eGFR measurement that is ≥80% of baseline; do not exceed the starting dose.

Monitor blood pressure every two weeks for the first month after initiating LUPKYNIS, and as clinically indicated thereafter [see Warnings and Precautions (5.4)] . For patients with BP >165/105 mmHg or with hypertensive emergency, discontinue LUPKYNIS and initiate antihypertensive therapy.

If the patient does not experience therapeutic benefit by 24 weeks, consider discontinuation of LUPKYNIS.

2.4 Dosage Recommendations in Patients with Renal and Hepatic Impairment

Use of LUPKYNIS is not recommended in patients with a baseline eGFR ≤45 mL/min/1.73 m^2 unless the benefit exceeds the risk; LUPKYNIS has not been studied in patients with a baseline eGFR ≤45 mL/min/1.73 m^2. If used in patients with severe renal impairment at baseline, the recommended starting dose is 15.8 mg twice a day [see Use in Specific Populations (8.6) and Clinical Pharmacology (12.3)] .

In patients with mild and moderate hepatic impairment (Child-Pugh A and Child-Pugh B), the recommended dose is 15.8 mg twice daily. LUPKYNIS is not recommended to be used in patients with severe hepatic impairment (Child-Pugh C) [see Use in Specific Populations (8.7) and Clinical Pharmacology (12.3)] .

2.5 Dosage Adjustments due to Drug Interactions

When co-administering LUPKYNIS with moderate CYP3A4 inhibitors (e.g., verapamil, fluconazole, diltiazem), reduce LUPKYNIS daily dosage to 15.8 mg in the morning and 7.9 mg in the evening. No dose adjustment of LUPKYNIS is recommended when LUPKYNIS is co-administered with mild CYP3A4 inhibitors [see Drug Interactions (7.1) and Clinical Pharmacology (12.3)] .

3 DOSAGE FORMS AND STRENGTHS

Capsules: 7.9 mg (voclosporin) oval, pink/orange in color, imprinted on one side with VCS in white ink.

4 CONTRAINDICATIONS

LUPKYNIS is contraindicated in:

- Patients concomitantly using strong CYP3A4 inhibitors (e.g., ketoconazole, itraconazole, clarithromycin) because these medications can significantly increase exposure to LUPKYNIS which may increase the risk of acute and/or chronic nephrotoxicity [see Warnings and Precautions (5.3), Drug Interactions (7.1), and Pharmacokinetics (12.3)] .
- Patients with a history of serious or severe hypersensitivity reaction, including anaphylaxis, to LUPKYNIS or any of its excipients [see Warnings and Precautions (5.8)] .

5 WARNINGS AND PRECAUTIONS

5.1 Lymphoma and Other Malignancies

Immunosuppressants, including LUPKYNIS, increase the risk of developing lymphomas and other malignancies, particularly of the skin. The risk appears to be related to the intensity and duration of immunosuppression rather than to the use of any specific agent. Examine patients for skin changes and advise to avoid or limit sun exposure and to avoid artificial UV light (tanning beds, sun lamps) by wearing protective clothing and using a broad spectrum sunscreen with a high protection factor (SPF 30 or higher).

5.2 Serious Infections

Immunosuppressants, including LUPKYNIS, increase the risk of developing bacterial, viral, fungal, and protozoal infections, including opportunistic infections. These infections may lead to serious, including fatal, outcomes. Viral infections reported include cytomegalovirus and herpes zoster infections.

Monitor for the development of infection. Consider the benefits and risks for the individual patient; use the lowest effective dose needed to maintain response.

5.3 Nephrotoxicity

LUPKYNIS, like other calcineurin-inhibitors, can cause acute and/or chronic nephrotoxicity. Nephrotoxicity was reported in clinical trials [see Adverse Reactions (6.1)] . Monitor eGFR regularly during treatment, and consider dose reduction or discontinuation in patients with decreases in eGFR from baseline [see Dosage and Administration (2.3)] ; persistent decrease of eGFR should be evaluated for chronic calcineurin-inhibitor nephrotoxicity.

Consider the risks and benefits of LUPKYNIS treatment in light of the patient’s treatment response and risk of worsening nephrotoxicity, including co-administration with drugs associated with nephrotoxicity. The risk for acute and/or chronic nephrotoxicity is increased when LUPKYNIS is concomitantly administered with drugs associated with nephrotoxicity.

5.4 Hypertension

Hypertension is a common adverse reaction of LUPKYNIS therapy and may require antihypertensive therapy [see Adverse Reactions (6.1)] . Some antihypertensive drugs can increase the risk for hyperkalemia [see Warnings and Precautions (5.6)] . Certain calcium-channel blocking agents (verapamil and diltiazem) may increase voclosporin blood concentrations and require dosage reduction of LUPKYNIS [see Dosage and Administration (2.5) and Drug Interactions (7.2)] .

Monitor blood pressure regularly during treatment and treat new-onset hypertension and exacerbations of pre-existing hypertension. If a patient experiences increases in blood pressure that cannot be managed with dose reduction of LUPKYNIS or other appropriate medical intervention, consider discontinuation of LUPKYNIS [see Dosage and Administration (2.3)] .

5.5 Neurotoxicity

LUPKYNIS, like other calcineurin-inhibitors, may cause a spectrum of neurotoxicities [see Adverse Reactions (6.1)] . The most severe neurotoxicities include posterior reversible encephalopathy syndrome (PRES), delirium, seizure, and coma; others include tremors, paresthesias, headache, mental status changes, and changes in motor and sensory functions. Monitor for neurologic symptoms and consider dosage reduction or discontinuation of LUPKYNIS if neurotoxicity occurs.

5.6 Hyperkalemia

Hyperkalemia, which may be serious and require treatment, has been reported with calcineurin inhibitors including LUPKYNIS [see Adverse Reactions (6.1)] . Concomitant use of agents associated with hyperkalemia (e.g., potassium-sparing diuretics, ACE inhibitors, angiotensin receptor blockers) may increase the risk for hyperkalemia. Monitor serum potassium levels periodically during treatment.

5.7 QTc Prolongation

LUPKYNIS prolongs the QTc interval in a dose-dependent manner after single dose administration at a dose higher than the recommended lupus nephritis therapeutic dose [see Clinical Pharmacology (12.2)] . The use of LUPKYNIS in combination with other drugs that are known to prolong QTc may result in clinically significant QT prolongation.

Certain circumstances may increase the risk of the occurrence of torsade de pointes and/or sudden death in association with the use of drugs that prolong the QTc interval, including (1) bradycardia; (2) hypokalemia or hypomagnesemia; (3) concomitant use of other drugs that prolong the QTc interval; and (4) presence of congenital prolongation of the QT interval.

5.8 Hypersensitivity Reactions

Postmarketing cases of hypersensitivity reactions, including anaphylaxis and angioedema, have been reported with LUPKYNIS. If signs or symptoms of a hypersensitivity reaction occur, discontinue LUPKYNIS; treat and monitor until signs and symptoms resolve [see Contraindications (4)] .

5.9 Immunizations

Avoid the use of live attenuated vaccines during treatment with LUPKYNIS (e.g., intranasal influenza, measles, mumps, rubella, oral polio, BCG, yellow fever, varicella, and TY21a typhoid vaccines).

Inactivated vaccines noted to be safe for administration may not be sufficiently immunogenic during treatment with LUPKYNIS.

5.10 Pure Red Cell Aplasia

Cases of pure red cell aplasia (PRCA) have been reported in patients treated with another calcineurin-inhibitor immunosuppressant. All of these patients reported risk factors for PRCA such as parvovirus B19 infection, underlying disease, or concomitant medications associated with PRCA. A mechanism for calcineurin-inhibitor-induced PRCA has not been elucidated. If PRCA is diagnosed, consider discontinuation of LUPKYNIS.

6 ADVERSE REACTIONS

The following clinically significant adverse reactions are described elsewhere in the labeling:

- Lymphoma and Other Malignancies [see Warnings and Precautions (5.1)]
- Serious Infections [see Warnings and Precautions (5.2)]
- Nephrotoxicity due to LUPKYNIS and Drug Interactions [see Warnings and Precautions (5.3)]
- Hypertension [see Warnings and Precautions (5.4)]
- Neurotoxicity [see Warnings and Precautions (5.5)]
- Hyperkalemia [see Warnings and Precautions (5.6)]
- QTc Prolongation [see Warnings and Precautions (5.7)]
- Hypersensitivity Reactions [see Warnings and Precautions (5.8)]
- Immunizations [see Warnings and Precautions (5.9)]
- Pure Red Cell Aplasia [see Warnings and Precautions (5.10)]

6.1 Clinical Trials Experience

Because clinical trials are conducted under widely varying conditions, adverse reaction rates observed in the clinical trials of a drug cannot be directly compared to rates in the clinical trials of another drug and may not reflect the rates observed in practice.

A total of 355 patients with LN were treated with voclosporin in the Phase 2 and 3 clinical studies with 224 exposed for at least 48 weeks, and 92 exposed for 3 years.

Patients in Study 1 were randomized to LUPKYNIS 23.7 mg twice a day or placebo. A proportion of patients (n=216, 60%) in Study 1 continued in Study 1 extension, a double-blinded continuation study, and these patients were observed for up to 2 additional years [see Clinical Studies (14)] . Patients in Study 2 were randomized to LUPKYNIS 23.7 mg twice a day, voclosporin 39.5 mg twice a day, or placebo.

Patients received background treatment with MMF 2 g daily and an IV bolus of corticosteroids followed by a pre-specified oral corticosteroid taper dosing schedule; LUPKYNIS dosing was adjusted based on eGFR and BP.

A total of 267 patients received at least 1 dose of LUPKYNIS 23.7 mg twice a day with 184 exposed for at least 48 weeks. A total of 88 patients received at least 1 dose of voclosporin 39.5 mg twice a day with 40 exposed for 48 weeks.

Table 1 lists common adverse reactions occurring in at least 3% of patients receiving LUPKYNIS and at an incidence at least 2% greater than placebo in Studies 1 and 2.

Table 1: Adverse Reactions in ≥3% of Patients Treated with LUPKYNIS 23.7 mg Twice a Day and ≥2% Higher than Placebo in Studies 1 and 2
Adverse Reaction | LUPKYNIS 23.7 mg twice a day (n=267) | Placebo (n=266)
Glomerular filtration rate decreased [See Specific Adverse Reactions below (Nephrotoxicity)] | 26% | 9%
Hypertension | 19% | 9%
Diarrhea | 19% | 13%
Headache | 15% | 8%
Anemia | 12% | 6%
Cough | 11% | 2%
Urinary tract infection | 10% | 6%
Abdominal pain upper | 7% | 2%
Dyspepsia | 6% | 3%
Alopecia | 6% | 3%
Renal Impairment | 6% | 3%
Abdominal pain | 5% | 2%
Mouth ulceration | 4% | 1%
Fatigue | 4% | 1%
Tremor | 3% | 1%
Acute kidney injury | 3% | 1%
Decreased appetite | 3% | 1%

Other adverse reactions reported in less than 3% of patients in the LUPKYNIS 23.7 mg group and at a 2% higher rate than in the placebo group through 48/52 weeks included gingivitis and hypertrichosis.

The overall profile of adverse events seen in Study 1 extension (representing 203 patient-years of additional exposure) were similar in both nature and severity to those seen in the first year of treatment (Study 1). The annual incidence of adverse reactions reduced each successive year in both treatment groups.

The integrated LN dataset is presented in the Specific Adverse Reactions section:

Placebo-controlled Studies: Studies 1 and 2 were integrated to represent safety through 48/52 weeks for placebo (n=266), LUPKYNIS 23.7 mg twice a day (n=267), and voclosporin 39.5 mg twice a day (n=88). Among patients from Study 1, 100 patients (56.2%) on placebo twice a day and 116 patients (64.8%) on LUPKYNIS 23.7 mg twice a day continued in a follow-on study period for up to 2 additional years (Study 1 extension), with safety assessments through a total of up to 3 years.

Exposure adjusted incidence rates were adjusted by study for all the adverse events reported in this section.

Specific Adverse Reactions

Infections

In the integrated Study 1 and Study 2 data sets, infections were reported in 146 patients (107.4 per 100 patient-years) treated with placebo, 166 patients (135.2 per 100 patient-years) treated with LUPKYNIS 23.7 mg, and 58 patients (167.5 per 100 patient-years) treated with voclosporin 39.5 mg twice a day. The most frequent infections were upper respiratory tract infections, urinary tract infections, viral upper respiratory tract infections, and herpes zoster.

Serious infections were reported in 27 patients (12.0 per 100 patient-years) treated with placebo, 27 patients (11.9 per 100 patient-years) treated with LUPKYNIS 23.7 mg, and 10 patients (14.4 per 100 patient-years) treated with voclosporin 39.5 mg twice a day. The most frequent serious infections were pneumonia, gastroenteritis, and urinary tract infections.

Opportunistic infections were reported in 2 patients (0.9 per 100 patient-years) treated with placebo, 3 patients (1.3 per 100 patient-years) treated with LUPKYNIS 23.7 mg, and 1 patient (1.4 per 100 patient-years) treated with voclosporin 39.5 mg twice a day. The most frequent opportunistic infections were cytomegalovirus chorioretinitis, cytomegalovirus infection, and herpes zoster cutaneous disseminated.

In Study 1 extension, infections and infestations were reported in 43 patients (32.3 per 100 patient-years) treated with placebo and 57 patients (41.4 per 100 patient-years) treated with LUPKYNIS 23.7 mg. There were 8 serious infections reported in both placebo treated patients (4.5 per 100 patient-years) and LUPKYNIS treated patients (3.9 per 100 patient-years).

Nephrotoxicity

In the integrated Study 1 and Study 2 data sets, glomerular filtration rate decreased was the most frequently reported adverse reaction, reported in 25 patients (11.3 per 100 patient-years) treated with placebo, 70 patients (37.1 per 100 patient-years) treated with LUPKYNIS 23.7 mg, and 27 patients (48.7 per 100 patient-years) treated with voclosporin 39.5 mg twice a day. In patients treated with LUPKYNIS 23.7 mg twice a day, decreases in glomerular filtration rate occurred within the first 3 months of LUPKYNIS treatment in 50/70 (71%), with 39/50 (78%) resolved or improved following dose modification, and of those 25/39 (64%) resolved or improved within 1 month [see Dosage and Administration (2.3)] . Decreases in glomerular filtration rate resulted in permanent discontinuation of LUPKYNIS in 10/70 (14%), and resolved in 4/10 (40%) 3 months after treatment discontinuation.

Renal adverse reactions (defined as renal impairment, acute kidney injury, blood creatinine increased, azotemia, renal failure, oliguria, and proteinuria) were reported in 22 patients (9.5 per 100 patient-years) treated with placebo, 26 patients (11.3 per 100 patient-years) treated with LUPKYNIS 23.7 mg, and 11 patients (16.5 per 100 patient-years) treated with voclosporin 39.5 mg twice a day.

Serious renal adverse reactions were reported in 9 patients (3.7 per 100 patient-years) treated with placebo, 13 patients (5.6 per 100 patient-years) treated with LUPKYNIS 23.7 mg, and 0 patients (0 per 100 patient-years) treated with voclosporin 39.5 mg twice a day. The most frequent serious renal adverse reactions were acute kidney injury and renal impairment.

In Study 1 extension, eGFR decreased was reported in 5 patients (2.8 per 100 patient-years) treated with placebo and 12 patients (6.1 per 100 patient-years) treated with LUPKYNIS 23.7 mg. Renal and urinary adverse events were reported in 10 patients (5.7 per 100 patient-years) treated with placebo and 21 patients (10.7 per 100 patient-years) treated with LUPKYNIS. Serious renal and urinary adverse events were reported in 5 patients (2.8 per 100 patient-years) treated with placebo and 2 patients (0.9 per 100 patient-years) treated with LUPKYNIS, and included lupus nephritis in both treatment groups.

Hypertension

In the integrated Study 1 and Study 2 data sets, hypertension was reported in 23 patients (10.3 per 100 patient-years) treated with placebo, 51 patients (25.2 per 100 patient-years) treated with LUPKYNIS 23.7 mg, and 16 patients (26.0 per 100 patient-years) treated with voclosporin 39.5 mg twice a day.

Serious hypertension was reported in 1 patient (0.4 per 100 patient-years) treated with placebo, 5 patients (2.1 per 100 patient-years) treated with LUPKYNIS 23.7 mg, and 2 patients (2.8 per 100 patient-years) treated with voclosporin 39.5 mg twice a day.

In Study 1 extension, hypertension was reported in 7 patients (4.0 per 100 patient-years) treated with placebo and 10 patients (4.9 per 100 patient-years) treated with LUPKYNIS 23.7 mg.

Neurotoxicity

In the integrated Study 1 and Study 2 data sets, nervous system disorders were reported in 44 patients (21.6 per 100 patient-years) treated with placebo, 74 patients (38.9 per 100 patient-years) treated with LUPKYNIS 23.7 mg, and 24 patients (42.5 per 100 patient-years) treated with voclosporin 39.5 mg twice a day. The most frequent neurological adverse reactions were headache, tremor, dizziness, post herpetic neuralgia, migraine, paresthesia, hypoaesthesia, seizure, tension headache, and disturbance in attention.

Serious nervous system disorders were reported in 2 patients (0.9 per 100 patient-years) treated with placebo, 9 patients (3.9 per 100 patient-years) treated with LUPKYNIS 23.7 mg, and 3 patients (4.3 per 100 patient-years) treated with voclosporin 39.5 mg twice a day. The most frequent serious neurological adverse reactions were headache, migraine, seizure, and posterior reversible encephalopathy syndrome.

In Study 1 extension, nervous system disorders (including headache) were reported in 8 patients (4.7 per 100 patient-years) treated with placebo and 14 patients (7.3 per 100 patient-years) treated with LUPKYNIS 23.7 mg.

Malignancy

In the integrated Study 1 and Study 2 data sets, malignancies were reported in 0 patients (0 per 100 patient-years) treated with placebo, 4 patients (1.7 per 100 patient-years) treated with LUPKYNIS 23.7 mg, and 0 patients (0 per 100 patient-years) treated with voclosporin 39.5 mg twice a day. These consisted of single occurrences of stage 0 cervical carcinoma, skin neoplasm, pyoderma gangrenosum, and breast tumor excision.

In Study 1 extension, there were no reports of malignancies in either treatment arm.

Hyperkalemia

In the integrated Study 1 and Study 2 data sets, hyperkalemia was reported in 2 patients (0.8 per 100 patient-years) treated with placebo, 5 patients (2.1 per 100 patient-years) treated with LUPKYNIS 23.7 mg, and 1 patient (1.4 per 100 patient-years) treated with voclosporin 39.5 mg twice a day.

In Study 1 extension, hyperkalemia was reported in 0 patients treated with placebo and 1 patient (0.5 per 100 patient-years) treated with LUPKYNIS 23.7 mg.

QT Prolongation

In the integrated Study 1 and Study 2 data sets, QT prolongation was reported in 0 patients (0 per 100 patient-years) treated with placebo, 2 patients (0.9 per 100 patient-years) treated with LUPKYNIS 23.7 mg, and 1 patient (1.4 per 100 patient-years) treated with voclosporin 39.5 mg twice a day.

In Study 1 extension, no patient treated with LUPKYNIS 23.7 mg reported QT prolongation.

6.2 Postmarketing Experience

The following adverse recations have been identified during post approval use of LUPKYNIS. Because these reactions are reported voluntarily from a population of uncertain size, it is not always possible to reliably estimate their frequency or establish a causal relationship to drug exposure:

- Hypersensitivity reactions, including anaphylaxis and angioedema [see Warnings and Precautions (5.8)]
- Nausea, vomiting

7 DRUG INTERACTIONS

7.1 Effect of Other Drugs on LUPKYNIS

Strong and Moderate CYP3A4 Inhibitors

Voclosporin is a sensitive CYP3A4 substrate. Co-administration with strong or moderate CYP3A4 inhibitors increases voclosporin exposure [see Clinical Pharmacology (12.3)] , which may increase the risk of LUPKYNIS adverse reactions. Co-administration of LUPKYNIS with strong CYP3A4 inhibitors (e.g., ketoconazole, itraconazole, clarithromycin) is contraindicated [see Contraindications (4)] . Reduce LUPKYNIS dosage when co-administered with moderate CYP3A4 inhibitors (e.g., verapamil, fluconazole, diltiazem) [see Dosage and Administration (2.5] . Avoid food or drink containing grapefruit when taking LUPKYNIS.

Strong and Moderate CYP3A4 Inducers

Voclosporin is a sensitive CYP3A4 substrate. Co-administration with strong or moderate CYP3A4 inducers decreases voclosporin exposure [see Clinical Pharmacology (12.3)] , which may decrease the efficacy of LUPKYNIS. Avoid co-administration of LUPKYNIS with strong or moderate CYP3A4 inducers.

7.2 Effect of LUPKYNIS on Other Drugs

Certain P-gp Substrates

Voclosporin is a P-gp inhibitor. Co-administration of voclosporin increases exposure of P-gp substrates [see Clinical Pharmacology (12.3)] , which may increase the risk of adverse reactions of these substrates. For certain P-gp substrates with a narrow therapeutic window, reduce the dosage of the substrate as recommended in its prescribing information, if needed.

OATP1B1 Substrates

Voclosporin is an inhibitor of OATP1B1 and OATP1B3 transporters. In one clinical study the concomitant administration of a single 40 mg dose of simvastatin with 23.7 mg BID voclosporin increased Cmax and AUC of the active metabolite simvastatin acid (an OATP1B1 substrate) by 3.1-fold and 1.8-fold, respectively [see Clinical Pharmacology (12.3)] . Monitor for adverse reactions such as myopathy and rhabdomyolysis when OATP1B1/OATP1B3 substrates (e.g., simvastatin, atorvastatin, pravastatin, rosuvastatin, pitavastatin, fluvastatin) are used concomitantly with LUPKYNIS and reduce the dosage of these substrates as recommended in their prescribing information. For example, when taking LUPKYNIS with simvastatin, limit the simvastatin dosage to 20 mg daily, or 40 mg daily for patients who have previously tolerated simvastatin 80 mg daily for at least one year without evidence of muscle toxicity.

8 USE IN SPECIFIC POPULATIONS

8.1 Pregnancy

Risk Summary

Avoid use of LUPKYNIS in pregnant women due to the alcohol content of the drug formulation. The available data on the use of LUPKYNIS in pregnant patients are insufficient to determine whether there is a drug-associated risk for major birth defects, miscarriage, or adverse maternal or fetal outcomes. There are risks to the mother and fetus associated with systemic lupus erythematosus (SLE) (see Clinical Considerations) .

LUPKYNIS may be used in combination with a background immunosuppressive therapy regimen that includes MMF. MMF used in pregnant women and men whose female partners are pregnant can cause fetal harm (major birth defects and miscarriage). Refer to the MMF prescribing information for more information on its use during pregnancy.

In animal reproductive studies, oral administration of either voclosporin or a 50:50 mixture of voclosporin and its cis-isomer was embryocidal and fetocidal in rats and rabbits at doses 15- and 1-times, respectively, the maximum recommended human dose (MRHD) of 23.7 mg twice a day, based on drug exposure AUC. There were no treatment-related fetal malformations or variations. Additional findings of reduced placental and fetal body weights occurred in rabbits at 0.1 to 0.3-times the MRHD and in rats at higher drug exposures. Voclosporin was transferred across the placenta in pregnant rats. For rats, but not all doses in rabbits, these effects were associated with maternal toxicity consisting of reductions in body weight gain. Dystocia was evident in a pre- and postnatal study in rats, but there were no effects of voclosporin on postnatal growth and development (see Data) .

The estimated background risk of major birth defects and miscarriage for the indicated population is unknown. All pregnancies have a background risk of birth defect, loss, or other adverse outcomes. In the U.S. general population, the background risk of major birth defects and miscarriage in clinically recognized pregnancies is 2% to 4% and 15% to 20%, respectively.

Clinical Considerations

Disease-Associated Maternal and/or Embryo/Fetal Risk

Pregnant women with SLE are at increased risk of adverse pregnancy outcomes, including worsening of the underlying disease, premature birth, miscarriage, and intrauterine growth restriction. Maternal LN increases the risk of hypertension and preeclampsia/eclampsia. Passage of maternal autoantibodies across the placenta may result in adverse neonatal outcomes, including neonatal lupus and congenital heart block.

Fetal/Neonatal adverse reactions

The formulation of LUPKYNIS contains alcohol (21.6 mg of dehydrated ethanol per capsule for a total daily dose of 129.4 mg/day). Published studies have demonstrated that alcohol is associated with fetal harm including central nervous system abnormalities, behavioral disorders and impaired intellectual development. There is no safe level of alcohol exposure in pregnancy; therefore, avoid use of LUPKYNIS in pregnant women.

Data

Animal Data

Voclosporin (90 to 95% trans-isomer) is the active ingredient in LUPKYNIS. Animal reproductive studies were primarily conducted with an approximate 50:50 mixture of voclosporin and its cis-isomer. Similarity of the toxicity effects of the 50:50 mixture and voclosporin was demonstrated in comparative toxicity studies with adult rats. Interconversion between cis and trans isomers was not detected with in vitro or in vivo studies.

In an embryofetal developmental study, pregnant rats were dosed orally, during the period of organogenesis from gestation days 6-17, with the 50:50 mixture of voclosporin and its cis-isomer, litter size was reduced due to increased fetal resorptions and deaths at drug exposures approximately 15-times the MRHD (on an AUC basis with a maternal oral dose of 25 mg/kg/day). Surviving fetuses had reduced placental weights and slightly reduced fetal weights. There were no treatment-related fetal malformations or variations with doses up to 15-times the MRHD, although reductions in ossification sites were observed in the metatarsal bones. This dose was associated with maternal toxicity based on decreased body weight gain. The no effect dose for both fetal and maternal effects occurred at a drug exposure approximately 7-times the MRHD (on an AUC basis with a maternal oral dose of 10 mg/kg/day).

Two embryofetal developmental studies were conducted in pregnant rabbits that received either the 50:50 mixture of voclosporin and its cis-isomer or voclosporin during the period of organogenesis from gestation days 6-18. Litter size was reduced due to increased fetal resorptions and deaths with 50:50 mixture at drug exposures approximately the MRHD (on an AUC basis with a maternal oral dose of 20 mg/kg/day). Increased resorptions were observed with voclosporin at 0.1-times the MRHD (on an AUC basis with a maternal dose of 20 mg/kg/day); however, litter size was not significantly affected. Decreased placental weights and fetal body weights were observed with the 50:50 mixture at doses 0.3-times the MRHD and higher (on an AUC basis with maternal oral doses of 10 mg/kg/day and higher). Decreased fetal body weights were observed with voclosporin at doses 0.1-times the MRHD and higher (on an AUC basis with maternal oral doses of 5 mg/kg/day and higher). There were no treatment-related malformations or variations. Both studies had reductions of ossification sites in the metacarpal bones with the 50:50 mixture at doses 2-times the MRHD, and the sternabrae and hyoid body and/or arches with voclosporin at doses 0.1-times the MRHD and higher. The high dose of 20 mg/kg/day 50:50 mixture of voclosporin was associated with maternal toxicity based on decreased body weight gains. These rabbit studies indicated that the toxicity of 50:50 mixture of voclosporin and its cis-isomer and voclosporin were qualitatively similar; however, voclosporin was more potent than the 50:50 mixture, consistent with its pharmacological potency. The no effect dose for the fetal effects of voclosporin occurred at a drug exposure approximately 0.01-times the MRHD (on an AUC basis with a maternal oral dose of 1 mg/kg/day).

In a pre-and post-natal developmental study, rats were dosed from gestation day 7 through lactation day 20 with a 50:50 mixture of voclosporin and its cis-isomer. Dystocia (delayed parturition) occurred at a dose 12-times the MRHD (on an AUC basis with a maternal oral dose of 25 mg/kg/day) that resulted in reductions of the mean number of total pups delivered and surviving pups per litter. This dose was associated with maternal toxicity based on decreased body weight gain. No adverse effects on dams or their pups were observed at doses 3-times the MRHD and lower (on an AUC basis with a maternal oral dose of 10 mg/kg/day). There were no effects on behavioral and physical development, or the reproductive performance of male or female pups. The no effect dose for delivery and pup survival was 10 mg/kg/day.

8.2 Lactation

Risk Summary

The available human data from a clinical lactation study detected small amounts of voclosporin in human milk. Following a single dose to lactating subjects, a fully breastfed infant was estimated to receive a daily infant dose of 0.00675 mg/kg, and relative infant dose of 1.4% the maternal weight-adjusted dose. No change is expected for infant exposure at steady state with maternal twice daily dosing (see Data) . Available data from the clinical study and published scientific literature are insufficient to determine the effects of LUPKYNIS on the breastfed infant or on milk production. The developmental and health benefits of breastfeeding should be considered along with the mother's clinical need for LUPKYNIS and any potential adverse effects on the breastfed infant from LUPKYNIS or from the medical condition of the mother.

Data

Following a single 23.7 mg dose of voclosporin in healthy lactating subjects, an average of 0.00472 mg voclosporin was excreted in breast milk. Data showed that the voclosporin milk to maternal blood exposure ratio was in the range of 0.42 to 0.95. Based on the infant milk intake of 200 mL/kg/day, the highest estimated voclosporin dose ingested by fully breastfed infant was 1.4% of maternal weight-adjusted dose, which equals estimated daily infant dose of 0.00675 mg/kg/day. At steady state following maternal twice daily dosing regimen, the percent of voclosporin dose present in breast milk is expected to be similar to that following maternal single dose.

8.3 Females and Males of Reproductive Potential

LUPKYNIS may be used in combination with a background immunosuppressive therapy regimen that includes MMF. If LUPKYNIS is administered with MMF, the information for MMF regarding pregnancy testing, contraception, and infertility also applies to this combination regimen. Refer to MMF prescribing information for additional information.

8.4 Pediatric Use

The safety and efficacy of LUPKYNIS in pediatric patients has not been established.

8.5 Geriatric Use

Clinical studies of LUPKYNIS did not include sufficient numbers of patients aged 65 and over to determine whether they respond differently from younger patients. Other reported clinical experience has not identified differences in responses between the elderly and younger patients. In general, dose selection for an elderly patient should be cautious, usually starting at the low end of the dosing range, reflecting the greater frequency of decreased hepatic, renal, or cardiac function, and of concomitant disease or other drug therapy.

8.6 Renal Impairment

Use of LUPKYNIS is not recommended in patients with a baseline eGFR ≤45 mL/min/1.73 m^2 unless the benefit exceeds the risk. If used in patients with severe renal impairment at baseline, LUPKYNIS should be used at a reduced dose [see Dosage and Administration (2.4)] . No dosage adjustment is recommended in patients with mild or moderate renal impairment at baseline [see Clinical Pharmacology (12.3)] . Monitor eGFR closely.

After initiating therapy, dosing adjustments should be made based on eGFR [see Dosage and Administration (2.3)] .

8.7 Hepatic Impairment

In patients with mild and moderate hepatic impairment (Child-Pugh A and Child-Pugh B), reduce the LUPKYNIS dosage [see Dosage and Administration (2.4)] . Avoid LUPKYNIS in patients with severe hepatic impairment (Child-Pugh C) [see Clinical Pharmacology (12.3)] .

10 OVERDOSAGE

Cases of accidental overdose have been reported with LUPKYNIS; symptoms may include tremor, headache, nausea and vomiting, infections, tachycardia, urticaria, lethargy, and increases in blood urea nitrogen, serum creatinine, and alanine aminotransferase levels.

No specific antidote to LUPKYNIS therapy is available. If overdose occurs, general supportive measures and symptomatic treatment should be conducted, including stopping treatment with LUPKYNIS and assessing blood urea nitrogen, serum creatinine, eGFR and alanine aminotransferase levels.

Consider contacting a poison center (1-800-222-1222) or medical toxicologist for advice and review of overdosage management recommendations.

11 DESCRIPTION

LUPKYNIS (voclosporin) capsules, a calcineurin-inhibitor immunosuppressant, is available for administration as soft gelatin capsules containing 7.9 mg voclosporin per capsule. Inactive ingredients include alcohol, Vitamin E polyethylene glycol succinate (NF), polysorbate 40 (NF), medium-chain triglycerides (NF), gelatin, sorbitol, glycerin, iron oxide yellow, iron oxide red, titanium dioxide, and water.

Voclosporin (90 to 95% trans-isomer) is the active ingredient in LUPKYNIS. Chemically, voclosporin is named: Cyclo{{(6E)-(2S,3R,4R)-3-hydroxy-4-methyl-2-(methylamino)-6,8-nonadienoyl}-L-2-aminobutyryl-N-methyl-glycyl-N-methyl-L-leucyl-L-valyl-N-methyl-L-leucyl-L-alanyl-D-alanyl-N-methyl-L-leucyl-N-methyl-L-leucyl-N-methyl-L-valyl}. The chemical structure of voclosporin is:

Voclosporin has an empirical formula of C63H111N11O12and a molecular weight of 1214.6 g/mole. It appears as white to off-white solid matter. At ambient temperature, voclosporin is freely soluble in acetone, acetonitrile, ethanol, and methanol, and practically insoluble in heptanes (USP). Voclosporin is practically insoluble (less than 0.1 g/L at 20ºC) in water and melts above 144ºC with decomposition.

12 CLINICAL PHARMACOLOGY

12.1 Mechanism of Action

LUPKYNIS is a calcineurin-inhibitor immunosuppressant. The mechanism of voclosporin suppression of calcineurin has not been fully established. Activation of lymphocytes involves an increase in intracellular calcium concentrations that bind to the calcineurin regulatory site and activate calmodulin binding catalytic subunit and through dephosphorylation activates the transcription factor, Nuclear Factor of Activated T-Cell Cytoplasmic (NFATc). The immunosuppressant activity results in inhibition of lymphocyte proliferation, T-cell cytokine production, and expression of T-cell activation surface antigens.

Studies in animal models also support a non-immunological role for calcineurin inhibition in kidney function to stabilize actin cytoskeleton and stress fibers in podocytes leading to increased podocyte integrity in glomeruli.

12.2 Pharmacodynamics

Calcineurin inhibition

Concentration-dependent calcineurin inhibition, measured as the percent of maximum calcineurin inhibition, was observed after oral administration of voclosporin twice daily in healthy volunteers. There is little or no lag time between the time to maximum drug concentration and the time to maximum calcineurin inhibition. Voclosporin inhibits calcineurin in a dose-dependent manner up to a maximum dose of 1.0 mg/kg.

Cardiac Electrophysiology

In a randomized, placebo- and active-controlled (moxifloxacin 400 mg), single dose study with parallel study design, dose-dependent QT prolonging effect was detected with LUPKYNIS in the dose range of 0.5–4.5 mg/kg (up to 9-fold coverage of the therapeutic exposure). Dose-dependent QT prolongation effect was observed with a time to maximum QTc increase occurring at 4–6-hour postdose across different dose levels. The maximum mean placebo-adjusted changes of QTcF from baseline after LUPKYNIS 0.5 mg/kg, 1.5 mg/kg, 3.0 mg/kg, and 4.5 mg/kg dose were 6.4 msec, 17.5 msec, 25.7 msec, and 34.6 msec, respectively.

In a separate, randomized, placebo-controlled, crossover study in 31 healthy subjects, an absence of large mean increases (i.e., >20 msec) was observed following 7 days of treatment with LUPKYNIS at 0.3, 0.5 and 1.5 mg/kg twice daily (approximately 6-fold coverage of the therapeutic exposure).

The mechanism for the QT prolonging effect as observed in the single-dose and multiple-dose studies is unknown.

12.3 Pharmacokinetics

The whole blood voclosporin pharmacokinetics increase in a greater than dose-proportional manner over the therapeutic range. With a twice daily dosing regimen, voclosporin achieves steady-state after 6 days and the accumulation is approximately 2-fold.

Absorption

The median Tmaxof voclosporin is 1.5 hours (1 to 4 hours) when administered on an empty stomach.

Effect of Food

Co-administration of voclosporin with food decreased both the rate and extent of absorption: with either low- or high-fat meals, Cmaxand AUC of voclosporin were reduced by 29% to 53% and 15% to 25%, respectively.

Distribution

The apparent volume of distribution (Vss/F) of voclosporin is 2,154 L.

Protein binding of voclosporin is 97%. Voclosporin partitions extensively into red blood cells and distribution between whole blood and plasma is concentration- and temperature-dependent.

Elimination

The mean apparent clearance at steady-state (CLss/F) of voclosporin is 63.6 L/h, and mean terminal half-life (t1/2) is approximately 30 hours (24.9 to 36.5 hours).

Metabolism

Voclosporin is predominantly metabolized by CYP3A4. Voclosporin is the major circulating component and the pharmacologic activity is mainly attributed to the parent molecule. A major metabolite in human whole blood represented 16.7% of total exposure and is about 8-fold less potent than the parent molecule.

Excretion

Following single oral administration of radiolabeled voclosporin 70 mg, 92.7% of the radioactivity was recovered in feces (including 5% as unchanged voclosporin), and 2.1% was recovered in urine (including 0.25% as unchanged voclosporin).

Specific Populations

There were no clinically significant differences in the pharmacokinetics of voclosporin based on age (18 to 66 years), sex, race (Caucasian, Black, Asian, other), or body weight (37 to 133 kg).

Patients with Renal Impairment

Voclosporin Cmax and AUC were similar in volunteers with mild (CLCr60 to 89 mL/min as estimated by Cockcroft-Gault) and moderate (CLCr30 to 59 mL/min) renal impairment compared to volunteers with normal renal function (CLCr≥90 mL/min). The Cmaxand AUC increased 1.5- and 1.7-fold, respectively, in volunteers with severe renal impairment (CLCr<30 mL/min). The effect of end-stage renal disease (ESRD) with or without hemodialysis on the pharmacokinetics of voclosporin is unknown.

Patients with Hepatic Impairment

Voclosporin Cmaxand AUC increased approximately 1.5- to 2.0-fold in volunteers with mild hepatic impairment (Child-Pugh A) or moderate hepatic impairment (Child-Pugh B). The effect of severe hepatic impairment (Child-Pugh C) on the pharmacokinetics of voclosporin is unknown.

Drug Interaction Studies

Effect of Other Drugs on LUPKYNIS

The effect of co‑administered drugs on the exposure of voclosporin is shown in Table 2.

Table 2: Change in Pharmacokinetics of Voclosporin in the Presence of Co-administered Drugs
Co-administered Drug | Regimen of Co-administered Drug | Ratio (90% CI)^1
Co-administered Drug | Regimen of Co-administered Drug | Cmax | AUC
Ketoconazole (strong CYP3A4 inhibitor) | 400 mg QD for 9 days | 6.45 (5.02, 8.29) | 18.55 (15.89, 21.65)
Verapamil (moderate CYP3A4 and strong P-gp inhibitor) | 80 mg TID for 10 days | 2.08 (1.89, 2.28) | 2.71 (2.56, 2.87)
Rifampin (strong CYP3A4 inducer) | 600 mg QD for 10 days | 0.32 (0.28, 0.37) | 0.13 (0.11, 0.15)
Notes: CI = Confidence interval; CYP = Cytochrome P450; P-gp = P-glycoprotein; QD = once daily; TID = every 8 hours.
^1Ratios for Cmaxand AUC compare co-administration of the medication with voclosporin vs. administration of voclosporin alone.

- Moderate CYP3A inhibitors:Co-administration of multiple doses of fluconazole or diltiazem is predicted to increase voclosporin Cmax and AUC0-12 approximately 2- and 3-fold, respectively.
- Weak CYP3A inhibitors:Co-administration of multiple doses of fluvoxamine and cimetidine is predicted to have minimal effects on voclosporin Cmax and AUC0-12.
- Moderate CYP3A inducers:Co-administration of multiple doses of efavirenz is predicted to decrease voclosporin Cmax and AUC0-12 by 61% and 70%, respectively.

In vitro, voclosporin is not a substrate for breast cancer resistance protein (BCRP) or organic anion transporting polypeptides OATP1B1 and OATP1B3.

Effect of LUPKYNIS on other Drugs

Voclosporin was studied on a background therapy that included MMF. Voclosporin 23.7 mg twice a day in patients with SLE (with or without LN) had no effect on mycophenolic acid (MPA) exposure. Also, clinical studies indicate that voclosporin is a weak inhibitor of P-gp and has no clinically relevant effects on the pharmacokinetics of the sensitive CYP3A4 substrate midazolam. However, voclosporin increased the systemic exposure of OATP1B1 substrated simvastatin and simvastatin acid. Summary of the results from clinical studies which evaluated the effect of voclosporin on other drugs is provided in Table 3.

Table 3: Change in Pharmacokinetics of Co-administered Drugs in the Presence of Voclosporin
Co-administered Drug | Multiple Dose Regimen of Voclosporin | Ratio (90% CI)^1
Co-administered Drug | Multiple Dose Regimen of Voclosporin | Cmax | AUC
MMF^2 (immunosuppressant) | 23.7 mg BID | 0.94 (0.77, 1.16) | 1.09 (0.94, 1.26)
Digoxin (P-gp substrate) | 0.4 mg/kg BID | 1.51 (1.40, 1.63) | 1.25 (1.19, 1.31)
Midazolam (sensitive CYP3A4 substrate) | 0.4 mg/kg BID | 0.89 (0.80, 0.99) | 1.02 (0.93, 1.12)
Simvastatin acid (OATP1B1 substrate)^3 | 23.7 mg BID | 3.10; (2.58, 3.73) | 1.84; (1.53, 2.20)
Notes: BID = twice daily; CI = Confidence interval; CYP = Cytochrome P450; MMF = mycophenolate mofetil; P-gp = P-glycoprotein.
^1 Ratios for Cmaxand AUC compare co-administration of the medication with voclosporin vs administration of the medication alone.
^2 Observed effect of voclosporin on MPA.
^3 Co-administration of voclosporin with simvastatin increased the Cmax of parent drug simvastatin by 1.6-fold but did not change AUC of simvastatin

Based on in vitro studies, voclosporin does not inhibit BCRP, CYP1A2, 2B6, 2C8, 2C9, 2C19, 2D6, or induce CYP1A2, 2B6, 3A4. Voclosporin is an inhibitor of OATP1B1 and OATP1B3.

14 CLINICAL STUDIES

The safety and efficacy of LUPKYNIS were investigated in Study 1 (NCT03021499), a 52-week, randomized, double-blind, placebo-controlled trial in patients with a diagnosis of systemic lupus erythematosus and with International Society of Nephrology / Renal Pathology Society (ISN/RPS) biopsy-proven active Class III or IV LN (alone or in combination with Class V LN) or Class V LN. Patients with Class III or IV LN (alone or in combination with Class V LN) were required to have a urine protein to creatinine (UPCR) ratio of ≥1.5 mg/mg; patients with Class V LN were required to have a UPCR of ≥2 mg/mg.

A total of 357 patients with LN were randomized in a 1:1 ratio to receive either LUPKYNIS 23.7 mg twice daily or placebo.

Patients in both arms received background treatment with MMF and corticosteroids as follows:

- Oral MMF at a target dose of 2 g/day (1 g twice a day). (Patients not already receiving MMF were started on MMF 500 mg twice a day with escalation to MMF 1 g twice a day after the first week.) Dose increases up to 3 g/day were allowed.
- Intravenous (IV) methylprednisolone on Day 1 and Day 2 at a dose of 500 mg/day (body weight ≥45 kg) or 250 mg/day (body weight <45 kg) followed by a reducing taper of oral corticosteroids [oral prednisone 25 mg/day (body weight ≥45 kg) or 20 mg/day (body weight <45 kg); tapered to achieve a target dose of 2.5 mg/day by Week 16].

Throughout the study, patients were prohibited from using immunosuppressants (other than MMF and hydroxychloroquine/chloroquine) and from changing/commencing angiotensin II receptor blockers (ARBs) or angiotensin converting enzyme (ACE) inhibitors.

Patients with baseline eGFR ≤45 mL/min/1.73 m^2 were not enrolled in this study.

Dosage was adjusted based on eGFR and BP in a pre-defined dosage adjustment protocol. Dosage adjustments should follow the dosage recommendations [see Dosage and Administration (2.3)] .

The median age of patients was 31 years (range 18 to 72). The proportion of women was 88%. Approximately 36.1% were White, 9.5% were Black, 30.5% were Asian, 1.1% were American Indian or Alaska Native, and 22.7% were multiple race or other. Approximately 32.5% were Hispanic or Latino.

The mean (SD) daily dose of voclosporin was 41.3 (±9.7) mg/day. The mean (SD) daily dose of MMF was 1.9 (±0.4) g/day; 9% received >2 but ≤3 g/day of MMF. The mean (SD) daily dose of IV methylprednisolone (on Day 1 was 495 (±90) mg/day and Day 2 was 487 (±55) mg/day). The mean (SD) starting oral corticosteroid dose (Day 3) was 22.8 (±4.8) mg/day; approximately 81% received ≤2.5 mg/day of oral corticosteroids at Week 16.

The distribution by kidney biopsy class was Class III or IV (60.8%), Class III or IV in combination with Class V (24.9%), and Class V (14.3%). Mean (SD) eGFR on entry was 91 (±30) mL/min/1.73 m^2. Mean (SD) UPCR on entry was 4.0 (±2.5) mg/mg.

The primary efficacy endpoint was the proportion of patients achieving complete renal response at Week 52. Complete renal response was defined as follows (both must be met):

- UPCR of ≤0.5 mg/mg, and
- eGFR ≥60 mL/min/1.73 m^2 or no confirmed decrease from baseline in eGFR of >20% or no treatment- or disease-related eGFR-associated event (defined as blood creatinine increased, creatinine renal clearance decreased, glomerular filtration rate decreased, serum creatinine increased, renal impairment, renal failure, or renal failure acute) at time of assessment.

In order to be considered a responder, the patient must not have received more than 10 mg prednisone for ≥3 consecutive days or for ≥7 days in total during Weeks 44 through 52. Patients who received rescue medication or withdrew from the study were considered non-responders.

A higher proportion of patients in the LUPKYNIS arm than the placebo arm achieved complete renal response at Week 52 (Table 4).

Table 4: Complete Renal Response at Week 52 (Study 1)
 | LUPKYNIS (N=179) | Placebo (N=178) | Odds Ratio
Primary Endpoint
Complete Renal Response at Week 52 [n (%)]a | 73 (40.8) | 40 (22.5) | 2.7 (95% CI: 1.6, 4.3); p<0.001
Components of Primary Endpoint
UPCR ≤0.5 mg/mg [n (%)] | 81 (45.3) | 41 (23.0) | 3.1 (95% CI: 1.9, 5.0)
eGFR ≥60 mL/min/1.73 m^2 or no confirmed decrease from baseline in eGFR of >20% or no treatment- or disease-related eGFR-associated adverse eventb at time of assessment [n (%)] | 147 (82.1) | 135 (75.8) | 1.5 (95% CI: 0.8, 2.5)
CI = Confidence interval; eGFR = Estimated glomerular filtration rate; UPCR = Urine protein to creatinine ratio.
a. In order to be considered a responder, the patient must not have received more than 10 mg prednisone for ≥3 consecutive days or for ≥7 days in total during Weeks 44 through 52. Patients who received rescue medication or withdrew from the study were considered non-responders.
b.Treatment- or disease-related eGFR-associated event is defined as blood creatinine increased, creatinine renal clearance decreased, glomerular filtration rate decreased, serum creatinine increased, renal impairment, renal failure, or renal failure acute.

A higher proportion of patients in the LUPKYNIS arm than the placebo arm achieved complete renal response at Week 24 (32.4% vs. 19.7%; odds ratio: 2.2; 95% CI: 1.3, 3.7). Time to UPCR of ≤0.5 mg/mg was shorter in the LUPKYNIS arm than the placebo arm (median time of 169 days vs. 372 days; hazard ratio: 2.0; 95% CI: 1.5, 2.7).

A 2-year extension study (NCT03597464) followed Study 1. After reconsenting, patients remained on blinded randomized treatment. From the LUPKYNIS arm, 116 patients (64.8%) and from the placebo arm, 100 patients (56.2%) agreed to continue treatment for up to a further 2 years. Over 52% of the 357 patients completed the study (LUPKYNIS 56.4%, placebo 47.8%); 51.4% of LUPKYNIS patients and 41.0% of placebo patients were still on study treatment at the end of study.

Among the 179 LUPKYNIS patients and 178 placebo patients who entered Study 1, 36 (20.1%) LUPKYNIS patients and 21 (11.8%) placebo patients were observed to achieve sustained complete renal response, where achieving sustained complete renal response is defined as achieving renal response at Month 12 and maintaining the renal response at each subsequent study visit through Month 36 (the end of the extension study). Thirty-nine (21.8%) LUPKYNIS subjects and 41 (23.0%) placebo subjects had missing data either at the end of the first year or by the end of the 2 year extension and therefore have an unknown status for sustained complete renal response.

13 NONCLINICAL TOXICOLOGY

13.1 Carcinogenesis, Mutagenesis, Impairment of Fertility

In a 2-year mouse carcinogenicity study, administration of voclosporin at oral doses of 3, 10, or 30 mg/kg/day resulted in an increased incidence of malignant lymphoma in high dose females (7.5 times the MRHD on an AUC basis) and a dose-responsive trend for increase in malignant lymphoma in males. Malignant lymphoma was considered drug related in mice. In a 2-year rat carcinogenicity study, oral administration of voclosporin at doses up to 1.25 mg/kg/day in males and 2.5 mg/kg/day in females (doses that result in approximately similar drug exposures in rats) resulted in no statistically significant increases of tumor incidences.

In a 39-week oral toxicology study with monkeys, malignant lymphomas occurred at a dose of 150 mg/kg/day (approximately 4- and 7-times MRHD based on AUC for male and female animals, respectively). [At this dose, monkeys experienced high levels of immunosuppression as indicated by maximum calcineurin inhibition levels (Emax) of greater than 80%.]

Voclosporin was not mutagenic or clastogenic in a standard battery of genetic toxicity studies that included the in vitro bacterial reverse mutation assay, in vitro Chinese hamster ovary cell chromosomal aberration assay, and in vivo rat micronucleus assay.

Voclosporin had no effect on fertility at doses up to 25 mg/kg/day in male and female rats (16- and 9-times MRHD based on AUC, respectively).

16 HOW SUPPLIED/STORAGE AND HANDLING

LUPKYNIS (voclosporin) capsules 7.9 mg are oval, pink/orange capsules, imprinted on one side with VCS in white ink, packed in cold-formed aluminum blisters, consisting of laminated backing and lidding materials that are thermo-sealed together. Four individual 3 × 5 blister strips are assembled into a cardboard wallet.

LUPKYNIS is available in:

- NDC 75626-001-01: Wallet containing 60 capsules
- NDC 75626-001-02: Carton containing three wallets (180 capsules)

LUPKYNIS is provided in child-proof packaging to avoid unintentional ingestion of study medication by children.

Store at controlled room temperature 20ºC to 25ºC (68ºF to 77ºF); excursions permitted to 15ºC to 30ºC (59ºF to 86ºF) [See USP Controlled Room Temperature].

Do not put LUPKYNIS in another container. Keep capsules in their original packaging until ready to be taken.

17 PATIENT COUNSELING INFORMATION

Advise the patient to read the FDA-approved patient labeling (Medication Guide).

Administration

Advise patients to:

- Swallow LUPKYNIS capsules whole, and not to open, crush, or divide LUPKYNIS capsules.
- Take LUPKYNIS on an empty stomach consistently as close to a 12-hour schedule as possible, and with a minimum of 8 hours between doses.
- If a dose is missed, take it as soon as possible within 4 hours after missing the dose. Beyond the 4-hour time frame, wait until the usual scheduled time to take the next regular dose. Do not double the next dose.
- Avoid eating grapefruit or drinking grapefruit juice while taking LUPKYNIS.

Development of Lymphoma and Other Malignancies

Inform patients that they are at an increased risk of developing lymphomas and other malignancies, particularly of the skin, due to immunosuppression. Advise patients to limit exposure to sunlight and ultraviolet (UV) light by wearing protective clothing and use a sunscreen with a high protection factor [see Boxed Warning and Warnings and Precautions (5.1)] .

Increased Risk of Infection

Inform patients that they are at an increased risk of developing a variety of infections, including opportunistic infections, due to immunosuppression and to contact their physician if they develop any symptoms of infection such as fever, sweats or chills, cough or flu-like symptoms, muscle aches, or warm, red, painful areas on the skin [see Boxed Warning and Warnings and Precautions (5.2)] .

Nephrotoxicity (Acute and/or Chronic)

Inform patients that LUPKYNIS can have toxic effects on the kidney that should be monitored. Advise patients to attend all visits and complete all blood tests ordered by their medical team [see Warnings and Precautions (5.3)] .

Hypertension

Inform patients that LUPKYNIS can cause high blood pressure which may require treatment with antihypertensive therapy. Advise patients to monitor their blood pressure [see Warnings and Precautions (5.4)] .

Neurotoxicity

Inform patients that they are at risk of developing adverse neurologic effects including seizure, altered mental status, and tremor. Advise patients to contact their physician should they develop vision changes, delirium, or tremors [see Warnings and Precautions (5.5)] .

Hyperkalemia

Inform patients that LUPKYNIS can cause hyperkalemia. Monitoring of potassium levels may be necessary, especially with concomitant use of other drugs known to cause hyperkalemia [see Warnings and Precautions (5.6)] .

Drug Interactions

Advise patients to tell their healthcare provider when they start or stop taking any concomitant medications. Strong CYP3A4 inhibitors (e.g., ketoconazole, itraconazole, clarithromycin) are contraindicated with LUPKYNIS, and other CYP3A4 enzyme modulating drugs can alter LUPKYNIS exposure [see Contraindications (4) and Drug Interactions (7.1)] .

Pregnancy

Inform female patients of the potential risk to a fetus and to avoid use of LUPKYNIS during pregnancy. When LUPKYNIS is administered in combination with MMF, refer patients to the MMF medication guide. Advise females to inform their healthcare provider if they are pregnant or become pregnant [see Use in Specific Populations (8.1, 8.3)] .

Lactation

Advise female patients to inform their healthcare provider if they are breastfeeding or intend to breastfeed while taking LUPKYNIS [see Use in Specific Populations (8.2)] .

Hypersensitivity Reactions

Inform patients of the potential risk of hypersensitivity reactions. Advise patients to stop taking LUPKYNIS and seek medical attention if signs or symptoms of a hypersensitivity reaction occur (such as swelling of face, lips, tongue, or throat; difficulty breathing or swallowing) [see Warnings and Precautions (5.8)] .

Immunizations

Inform patients that LUPKYNIS can interfere with the usual response to immunizations and that they should avoid live vaccines [see Warnings and Precautions (5.9)] .

Manufactured for:

Aurinia Pharmaceuticals Inc.
#140, 14315 - 118 Avenue
Edmonton, AB T5L4S6
Canada

Distributed by:

Aurinia Pharma U.S., Inc.
77 Upper Rock Circle
Suite 700
Rockville, MD 20850
USA

SPL MEDGUIDE SECTION

Medication Guide
LUPKYNIS™ (loop kye’ nis)
(voclosporin) capsules, for oral use

Read this Medication Guide before you start taking LUPKYNIS and each time you get a refill. There may be new information. This information does not take the place of talking with your healthcare provider about your medical condition or your treatment. If you have any questions about LUPKYNIS, ask your healthcare provider or pharmacist.

What is the most important information I should know about LUPKYNIS?
LUPKYNIS can cause serious side effects, including:

- Increased risk of cancer.People who take LUPKYNIS have an increased risk of getting certain kinds of cancer, including skin cancer and cancer of the lymph glands (lymphoma).
- Increased risk of infection.LUPKYNIS is a medicine that affects your immune system. LUPKYNIS can lower the ability of your immune system to fight infections. Serious infections can happen in people receiving LUPKYNIS that can lead to hospitalizations and can cause death. Call your healthcare provider right away if you have symptoms of an infection such as:

- fever

- cough or flu-like symptoms

- warm, red, or painful areas on your skin

- sweats or chills

- muscle aches

See “What are the possible side effects of LUPKYNIS?” for more information about side effects.

What is LUPKYNIS?

- LUPKYNIS is a prescription medicine used with other medicines to treat adults with active lupus nephritis.
- LUPKYNIS should not be taken with a medicine called cyclophosphamide. Talk with your healthcare provider if you are not sure if you take this medicine.

Do not take LUPKYNIS:

- with medicines known as strong CYP3A4 inhibitors such as ketoconazole, itraconazole, and clarithromycin.
- if you have a history of allergic reactions to voclosporin or any of the ingredients in LUPKYNIS. See the end of this Medication Guide for a complete list of ingredients in LUPKYNIS.

Before you take LUPKYNIS, tell your healthcare provider about all your medical conditions, including if you:

- plan to receive any vaccines. You should not receive any live vaccines during treatment with LUPKYNIS. Ask your healthcare provider if you are not sure if your vaccine is a live vaccine. Other vaccines may not work as well during treatment with LUPKYNIS.
- have or have had liver, kidney, or heart problems.
- have high blood pressure.
- are pregnant or plan to become pregnant when taking LUPKYNIS. LUPKYNIS may harm your unborn baby.
  - When taking LUPKYNIS in combination with mycophenolate mofetil, you should also read the Medication Guide for mycophenolate mofetil for important pregnancy information.
- are breastfeeding or plan to breastfeed. LUPKYNIS can pass into breastmilk. You and your healthcare provider should decide if you will take LUPKYNIS while you are breastfeeding.

Tell your healthcare provider about all the medicines you take, including prescription and over-the-counter medicines, vitamins, and herbal supplements. LUPKYNIS may affect the way other medicines work, and other medicines may affect how LUPKYNIS works.

How should I take LUPKYNIS?

- Take LUPKYNIS exactly as your healthcare provider tells you to take it.
- Your healthcare provider may change your dose, if needed. Do not stop taking or change your dose of LUPKYNIS without talking to your healthcare provider.
- Swallow LUPKYNIS capsules whole. Do not break, crush, chew or dissolve LUPKYNIS capsules before swallowing. If you cannot swallow LUPKYNIS capsules whole, tell your healthcare provider.
- Take LUPKYNIS on an empty stomach, either 1 hour before or 2 hours after a meal and as close to 12-hours between doses as possible. Do not take your doses of LUPKYNIS less than 8 hours apart. If a dose is missed, take it as soon as possible within 4 hours after missing the dose. If more than 4 hours has passed, skip the missed dose and take the next dose at the regular time. Do not take 2 doses at the same time.
- If you take too much LUPKYNIS, call your healthcare provider or go to the nearest hospital emergency room right away.

What should I avoid while taking LUPKYNIS?

- Live vaccines such as flu vaccine through your nose, measles, mumps, rubella, polio by mouth, BCG (TB vaccine), yellow fever, chicken pox (varicella), or typhoid.
- Exposure to sunlight and UV light such as tanning machines. Wear protective clothing and use a sunscreen.
- You should not eat grapefruit or drink grapefruit juice while taking LUPKYNIS.

What are the possible side effects of LUPKYNIS?
LUPKYNIS may cause serious side effects, including:

- See “ What is the most important information I should know about LUPKYNIS?”
- kidney problems.Kidney problems are common side effects of LUPKYNIS and may be serious. Your healthcare provider may do certain tests to check your kidney function while you take LUPKYNIS.
- high blood pressure.High blood pressure is a common side effect of LUPKYNIS and may be serious. Your healthcare provider will monitor your blood pressure while you take LUPKYNIS and may ask you to check your blood pressure at home.
- nervous system problems.Nervous system problems are a common side effect of LUPKYNIS and may be serious. Call your healthcare provider or go to the nearest hospital emergency room right away if you get any of these symptoms while taking LUPKYNIS. These could be signs of serious nervous system problems:

- confusion

- numbness and tingling

- seizures

- changes in alertness

- headache

- vision changes

- muscle tremors

- high levels of potassium in your blood. Your healthcare provider may do certain tests to check your potassium levels while you take LUPKYNIS.
- a serious heart rhythm problem (QT prolongation).
- allergic reactions. Allergic reactions, including a severe allergic reaction called anaphylaxis, can happen after taking LUPKYNIS. Stop taking LUPKYNIS and get emergency medical help right away if you have any of the following symptoms of an allergic reaction:

- swelling on the face, lips, tongue, or throat

- trouble breathing or swallowing

- rash, hives, or itching

- fast heartbeat

- fainting, dizziness, feeling lightheaded

- chest pain

- severe low red blood cell count (anemia).

The most common side effects of LUPKYNIS are:

- diarrhea

- urinary tract infection

- heartburn

- headache

- stomach pain

- loss of hair (alopecia)

- cough

These are not all the possible side effects of LUPKYNIS.
Call your healthcare provider for medical advice about side effects. You may report side effects to FDA at 1-800-FDA-1088.
You may also report side effects to www.fda.gov/medwatch.

How should I store LUPKYNIS?

- Store LUPKYNIS at room temperature between 68⁰F to 77⁰F (20⁰C to 25⁰C).
- Do not put LUPKYNIS in another container. Keep capsules in their original package until you are ready to take them.
- Keep LUPKYNIS and all medicines out of the reach of children.

General information about the safe and effective use of LUPKYNIS
Medicines are sometimes prescribed for purposes other than those listed in a Medication Guide. Do not use LUPKYNIS for a condition for which it was not prescribed. Do not give LUPKYNIS to other people, even if they have the same symptoms that you have. It may harm them. You can ask your pharmacist or healthcare provider for information about LUPKYNIS that is written for healthcare professionals.

What are the ingredients in LUPKYNIS?
Active ingredient: voclosporin
Inactive ingredients:alcohol, Vitamin E polyethylene glycol succinate, polysorbate 40, medium-chain triglycerides, gelatin
Manufactured for: Aurinia Pharmaceuticals Inc., Edmonton, AB T5L 4S6 Canada
Distributed by: Aurinia Pharma U.S., Inc., Rockville, MD 20850 USA
For more information, go to www.LUPKYNIS.com or call 1-833-AURINIA

This Medication Guide has been approved by the U.S. Food and Drug Administration Issued: 10/2025

PACKAGE LABEL PRINCIPAL DISPLAY PANEL SECTION

Wallet: 60 Capsules

NDC 75626-001-01

PACKAGE LABEL PRINCIPAL DISPLAY PANEL SECTION

Carton: 180 Capsules

NDC 75626-001-02